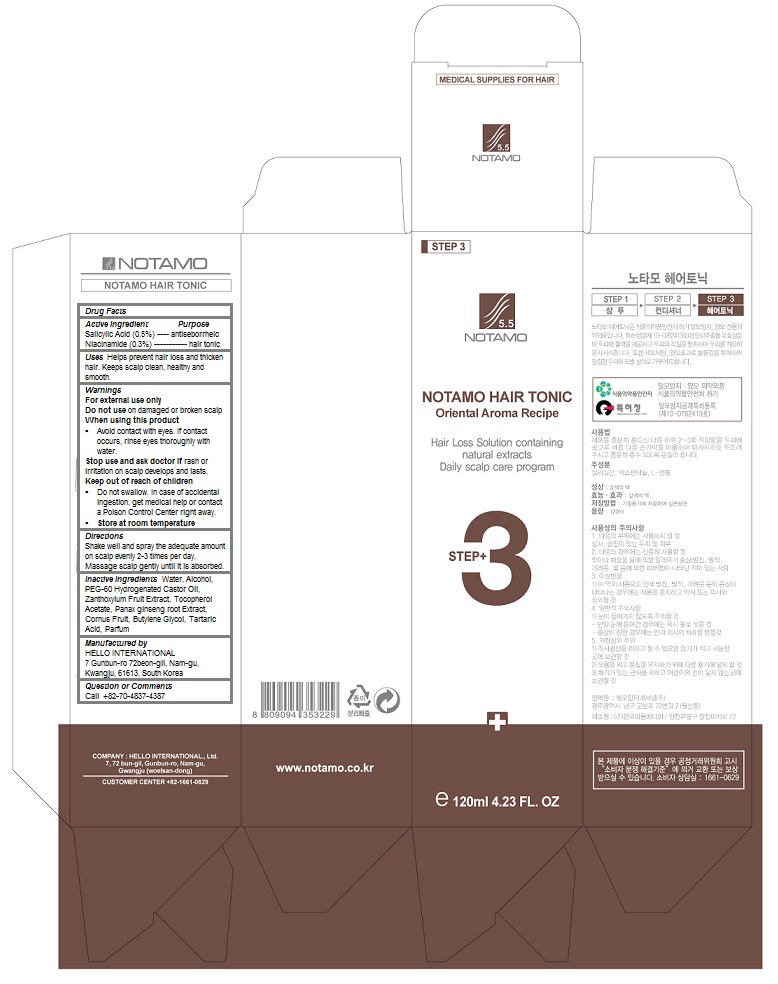 DRUG LABEL: Notamo Hair Tonic
NDC: 69709-104 | Form: LIQUID
Manufacturer: HELLO INTERNATIONAL
Category: otc | Type: HUMAN OTC DRUG LABEL
Date: 20160307

ACTIVE INGREDIENTS: Salicylic Acid 0.005 1/120 mL; Niacinamide 0.003 1/120 mL
INACTIVE INGREDIENTS: WATER; ALCOHOL; PEG-60 HYDROGENATED CASTOR OIL; .ALPHA.-TOCOPHEROL ACETATE; ASIAN GINSENG; CORNUS OFFICINALIS FRUIT; Butylene Glycol; Tartaric Acid

Notamo Hair Tonic